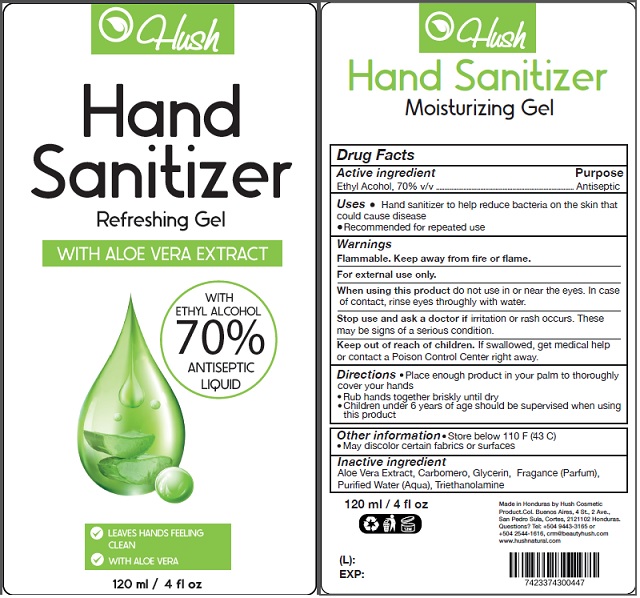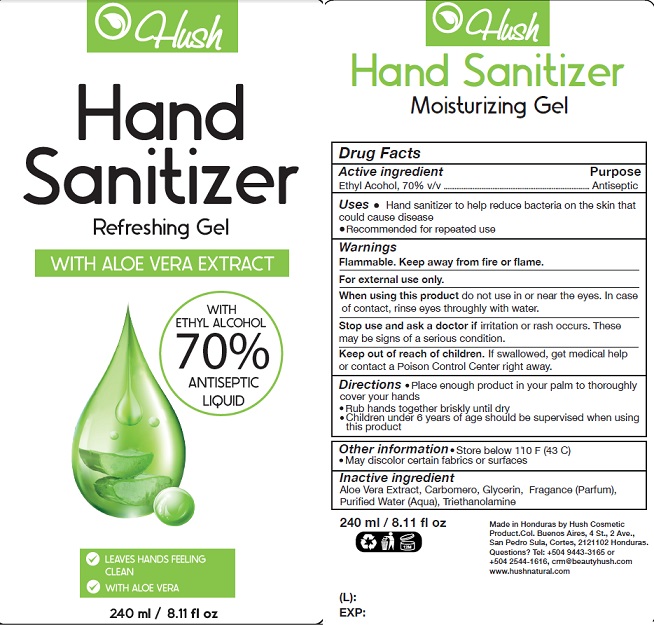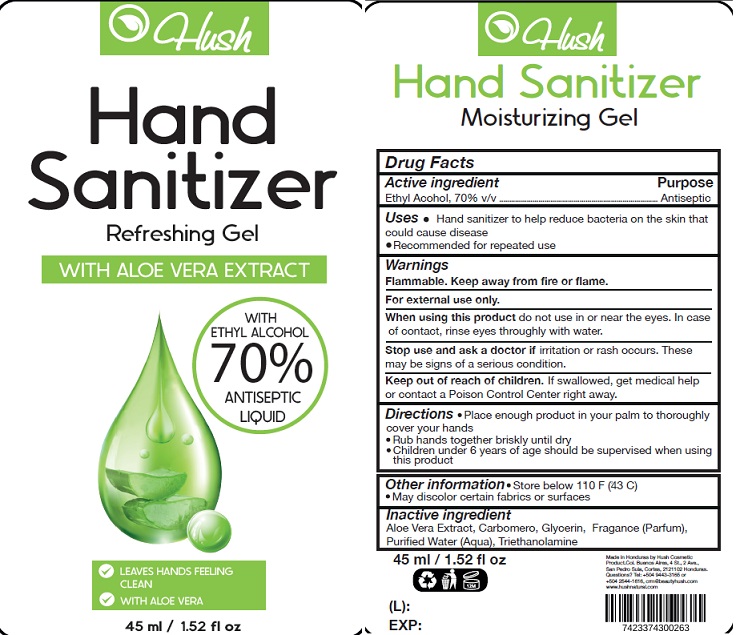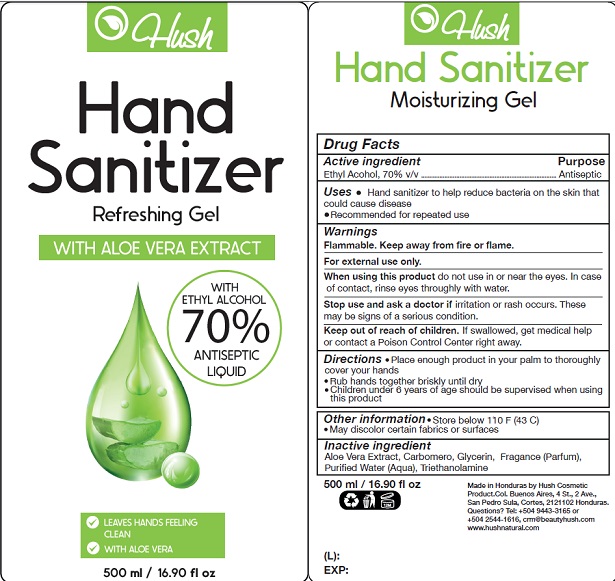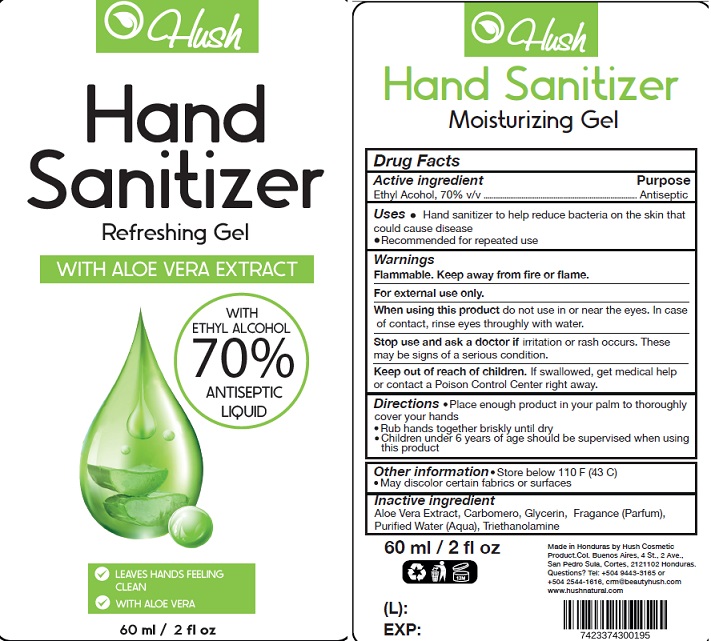 DRUG LABEL: Hush hand sanitizer with aloe vera extract
NDC: 78442-001 | Form: GEL
Manufacturer: Hush Cosmetic Products SRL
Category: otc | Type: HUMAN OTC DRUG LABEL
Date: 20210817

ACTIVE INGREDIENTS: ALCOHOL 70 mL/100 mL
INACTIVE INGREDIENTS: CARBOMER HOMOPOLYMER TYPE C (ALLYL PENTAERYTHRITOL CROSSLINKED); TROLAMINE; GLYCERIN; ALOE VERA LEAF; WATER

Active Ingredient

Ethyl Acohol, 70% v/v

Purpose

Antiseptic

Uses

Hand Sanitizer to help reduce bacteria that potentially can cause disease.

Recommended for repeated use.

Warnings

Flammable. Keep away from heat or flame.

For external use only.

When using this product do not use in or near the eyes. In case of contact, rinse eyes throughly with water.

Stop use and ask a doctor if irritation or rash occurs. These may be signs of a serious condition.

Keep out of reach of children. If swallowed, get medical help or contact a Poison Control Center right away.

Directions

- Place enough product on hands to cover all surfaces.
- Rub hands together until dry.
- Children under 6 years of age should be supervised when using this product.

Other information

- Store below 110^0F (43^0C)
- May discolor certain fabrics or surfaces

Inactive ingredients

Aloe Vera Extract, Carbomero, Glycerin, Fragance (Parfum), Purified Water (Aqua), Triethanolamine

Package Label - Principal Display Panel

45 mL Label

60 mL Label

120 mL Label

240 mL Label

500 mL label